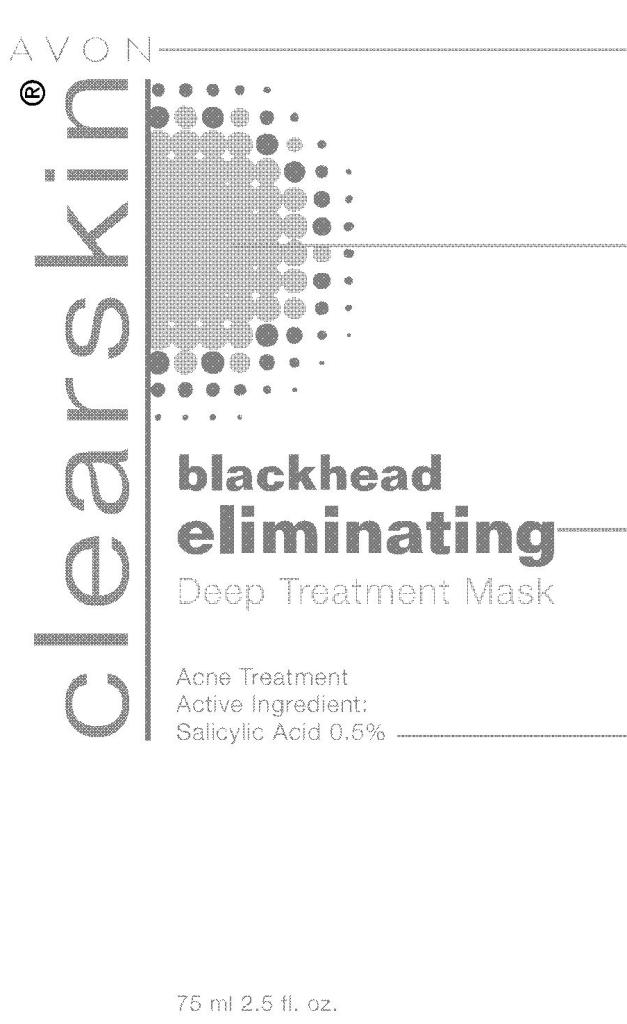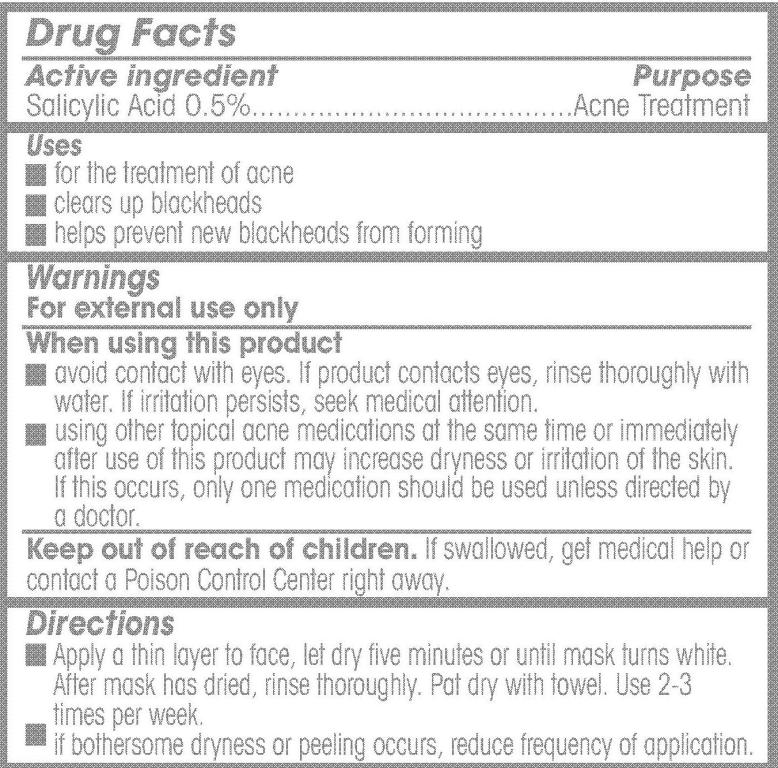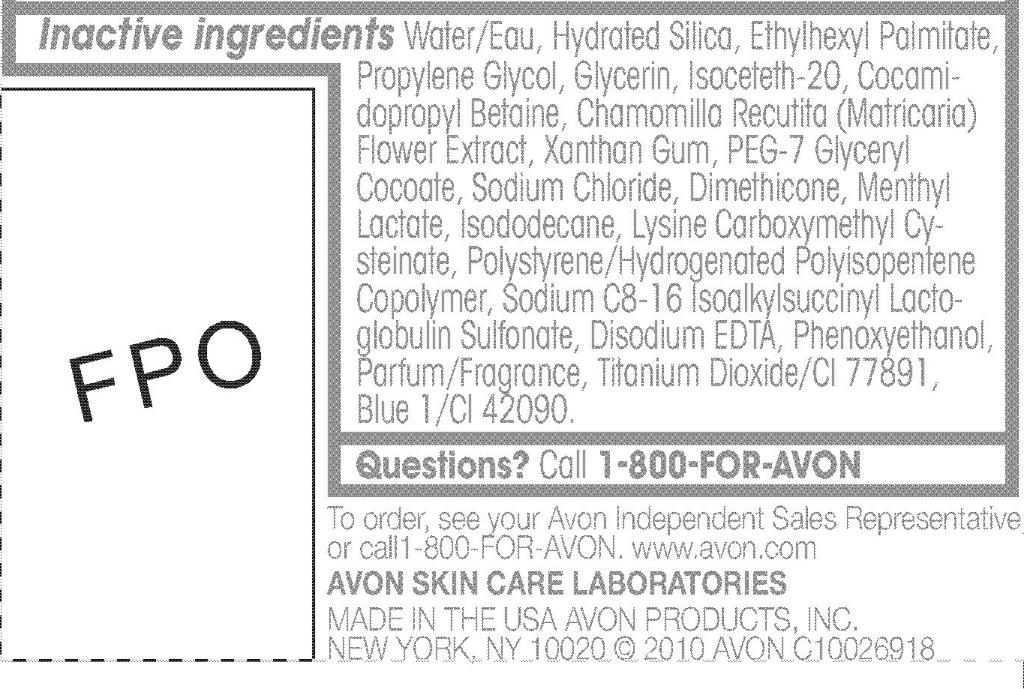 DRUG LABEL: Clearskin
NDC: 10096-0184 | Form: PASTE
Manufacturer: New Avon LLC
Category: otc | Type: HUMAN OTC DRUG LABEL
Date: 20160209

ACTIVE INGREDIENTS: Salicylic Acid 5 mg/1 mL

Drug Facts

Active ingredient

Salicylic Acid 0.5%........................

Uses

- for the treatment of acne
- clears up blackheads
- helps prevent new blackheads from forming

Warnings
For external use only.

When using this product

- avoid contact with eyes. If product contacts eyes, rinse thoroughly with water. If irritation persists, seek medical attention.
- using other topical acne medications at the same time or immediately after use of this product may increase dryness or irritation of the skin. If this occurs, only one medication should be used unless directed by a doctor.

Keep out of reach of children. If swallowed, get medical help or
contact a Poison Control Center right away.

Directions

- Apply a thin layer to face, let dry five minutes or until mask turns white. After mask has dried, rinse thoroughly. Pat dry with towel. Use 2-3 times per week.
- if bothersome dryness or peeling occurs, reduce frequency of application.

Inactive ingredients Water/Eau, Hydrated Silica, Ethylhexyl Palmitate,
Propylene Glycol, Glycerin, Isoceteth-20, Cocamidopropyl
Betaine, Chamomilla Recutita (Matricaria)
Flower Extract, Xanthan Gum, PEG-7 Glyceryl
Cocoate, Sodium Chloride, Dimethicone, Menthyl
Lactate, Isododecane, Lysine Carboxymethyl Cysteinate,
Polystyrene/Hydrogenated Polyisopentene
Copolymer, Sodium C8-16 Isoalkylsuccinyl Lactoglobulin
Sulfonate, Disodium EDTA, Phenoxyethanol,
Parfum/Fragrance, Titanium Dioxide/CI 77891,
Blue 1/CI 42090.

Questions? Call 1-800-FOR-AVON